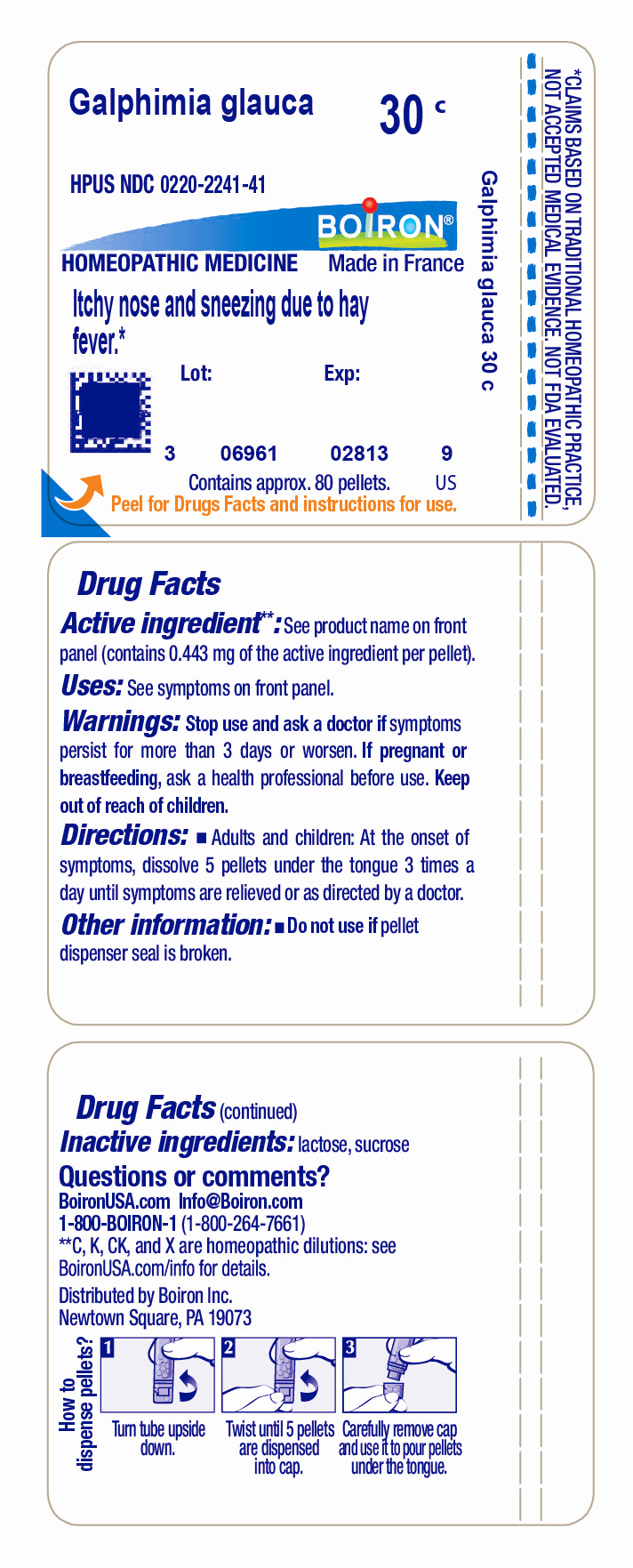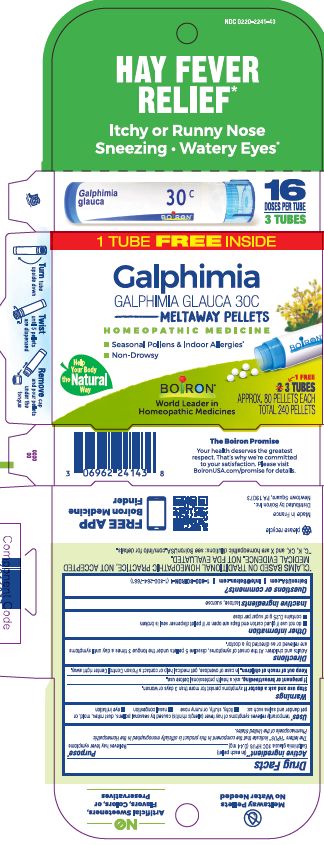 DRUG LABEL: Galphimia glauca
NDC: 0220-2241 | Form: PELLET
Manufacturer: Boiron
Category: homeopathic | Type: HUMAN OTC DRUG LABEL
Date: 20230220

ACTIVE INGREDIENTS: GALPHIMIA GLAUCA FLOWERING TOP 30 [hp_C]/30 [hp_C]
INACTIVE INGREDIENTS: LACTOSE, UNSPECIFIED FORM; SUCROSE

Galphimia glauca 30C

Active ingredient** (in each pellet)

Galphimia glauca 30C HPUS (0.44 mg)

Purpose*

Relieves hay fever symptoms

Uses*

Box - temporarily relieves symptoms of hay fever (allergic rhinitis) caused by seasonal pollens, dust mites, mold, or pet dander and saliva such as:

- itchy, stuffy, or runny nose
- nasal congestion
- eye irritation

Tube- Itchy Nose And Sneezing Due To Hay Fever*

Stop use and ask a doctor if symptoms persist for more than 3 days or worsen.

PREGNANCY OR BREAST FEEDING

If pregnant or breastfeeding, ask a health professional before use.

Keep out of reach of children. In case of overdose, get medical help or contact a Poison Control Center right away.

DOSAGE AND ADMINISTRATION

Adults and children: At the onset of symptoms, dissolve 5 pellets under the tongue 3 times a day until symptoms are relieved or as directed by a doctor.

Box-

- do not use if glued carton end flaps are open or if pellet dispenser seal is broken
- contains 0.25 g of sugar per dose

Hay Fever Relief*

Itchy or Runny Nose Sneezing Watery Eyes*

Turn the tube upside down

Twist until 5 pellets are dispensed

Remove cap and pour pellets under the tongue

3 Tubes

Approx. 80 Pellets Each

Total 240 Pellets

16 Doses per tube

Seasonal Pollens & Indoor Allergies*

Non-Drowsy

Tube-

Do not use if pellet dispenser seal is broken.
Contains approx 80 pellets.
How to dispense pellets? Turn tube upside down. Twist until 5 pellets are dispensed into cap. Carefully remove the cap and use it to pour pellets under the tongue.

*CLAIMS BASED ON TRADITIONAL HOMEOPATHIC PRACTICE NOT ACCEPTED MEDICAL EVIDENCE. NOT FDA EVALUATED.
*C,K,CK, and X are homeopathic dilutions: see BoironUSA.com/info for details.

INACTIVE INGREDIENT

lactose, sucrose

QUESTIONS

1-800-BOIRON-1 (1-800-264-7661),
BoironUSA.com Info@boiron.com
Distributed by Boiron, Inc. Newtown Square, PA 19073